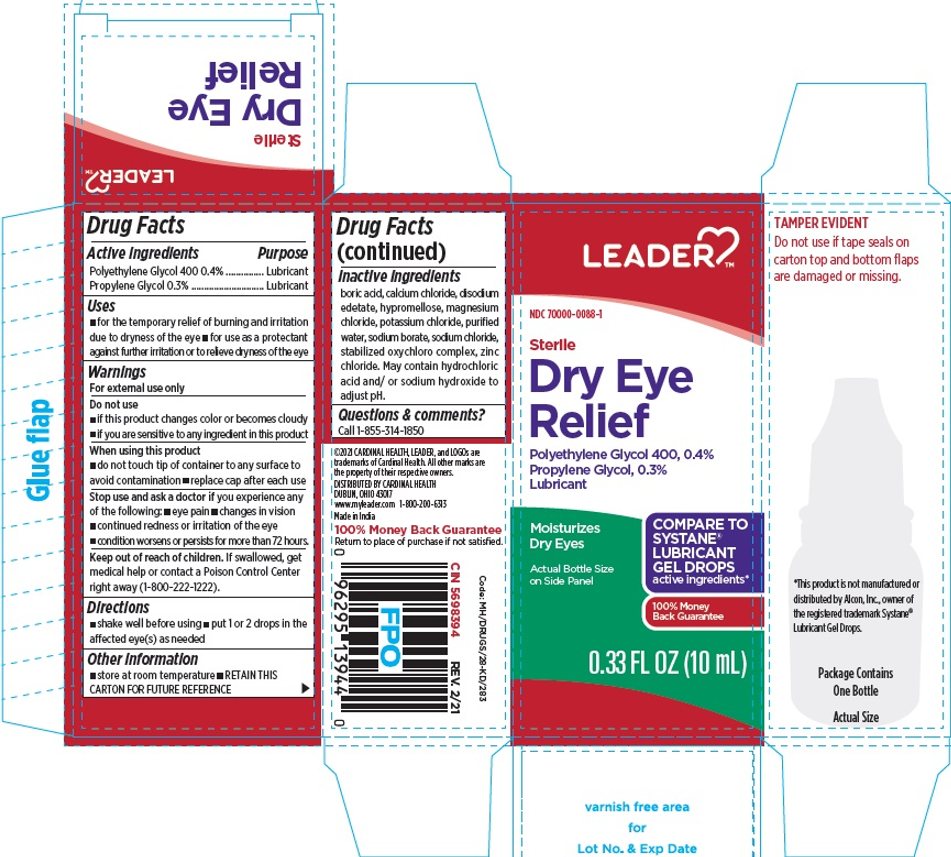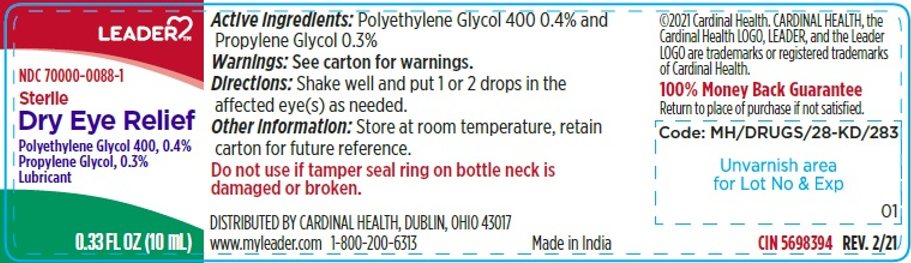 DRUG LABEL: Dry eye relief
NDC: 70000-0088 | Form: GEL
Manufacturer: CARDINAL HEALTH 110, LLC. DBA LEADER
Category: otc | Type: HUMAN OTC DRUG LABEL
Date: 20250912

ACTIVE INGREDIENTS: POLYETHYLENE GLYCOL 400 4 mg/1 mL; PROPYLENE GLYCOL 3 mg/1 mL
INACTIVE INGREDIENTS: BORIC ACID; CALCIUM CHLORIDE; EDETATE DISODIUM; HYPROMELLOSE, UNSPECIFIED; MAGNESIUM CHLORIDE; POTASSIUM CHLORIDE; WATER; SODIUM BORATE; SODIUM CHLORIDE; SODIUM CHLORITE; ZINC CHLORIDE

Sterile Dry eye Relief

ACTIVE INGREDIENT

Active Ingredients | Purpose
Polyethylene Glycol 400 0.4% | Lubricant
Propylene Glycol 0.3% | Lubricant

Uses

- for the temporary relief of burning and irritation due to dryness of the eye
- for use as a protectant against further irritation or to relieve dryness of the eye

Warnings

For external use only

Do not use

- if this product changes color or becomes cloudy
- if you are sensitive to any ingredient in this product

When using this product

- do not touch tip of container to any surface to avoid contamination
- replace cap after each use

Stop use and ask a doctor if you experience any of the following:

- you feel eye pain
- changes in vision
- continued redness or irritation of the eye
- condition worsens or persists for more than 72 hours

Keep out of reach of children. If swallowed, get medical help or contact a Poison Control Center right away.

Directions

- shake well before using
- put 1 or 2 drops in the affected eye(s) as needed

Other information

- store at room temperature

Inactive ingredients

boric acid, edetate disodium , potassium chloride, mangnesium chloride , sodium chloride, sodium borate , purified water. May contain hydrochloric acid and/or sodium hydroxide to adjust pH.

.

TAMPER EVIDENT

Do not use if tape seals on carton top and bottom flaps are damaged or missing.

*This product is not manufactured or distributed by Alcon, Inc., owner of the registered trademark Systane® Lubricant Gel Drops.

DISTRIBUTED BY CARDINAL HEALTH

DUBLIN, OHIO 43017

www.myleader.com 1-800-200-9313

Made in India

100% Money back Guarantee

Return to place of purchase if not satisfied.

Code: MH/DRUGS/28-KD/283

CIN 5698394 | REV. 2/21

Principal Display Panel

LEADER®

NDC 70000-0088-1

Sterile

Dry Eye Relief

Polyethylene Glycol 400, 0.4%

Propylene Glycol, 0.3%

Lubricant

0.33 FL OZ (10 mL)

Principal Display Panel

LEADER®

NDC 70000-0088-1

Sterile

Dry Eye

Relief

Polyethylene Glycol 400, 0.4%

Propylene Glycol, 0.3%

Lubricant

Moisturizes Dry Eyes

Actual Bottle Size on Side Panel

COMPARE TO SYSTANE® LUBRICANT GEL DROPS active ingredients*

100% Money Back Guarantee

0.33 FL OZ (10 mL)